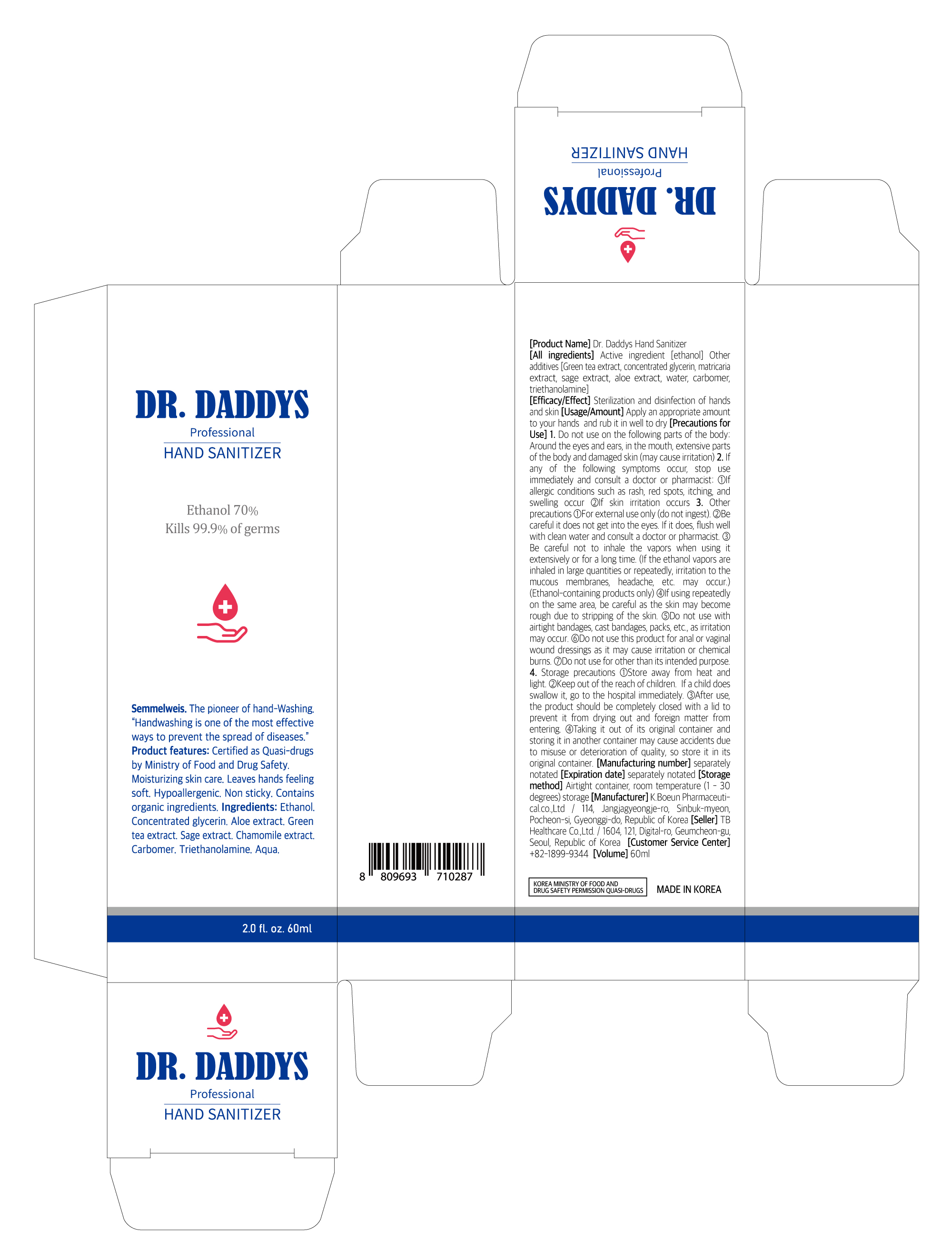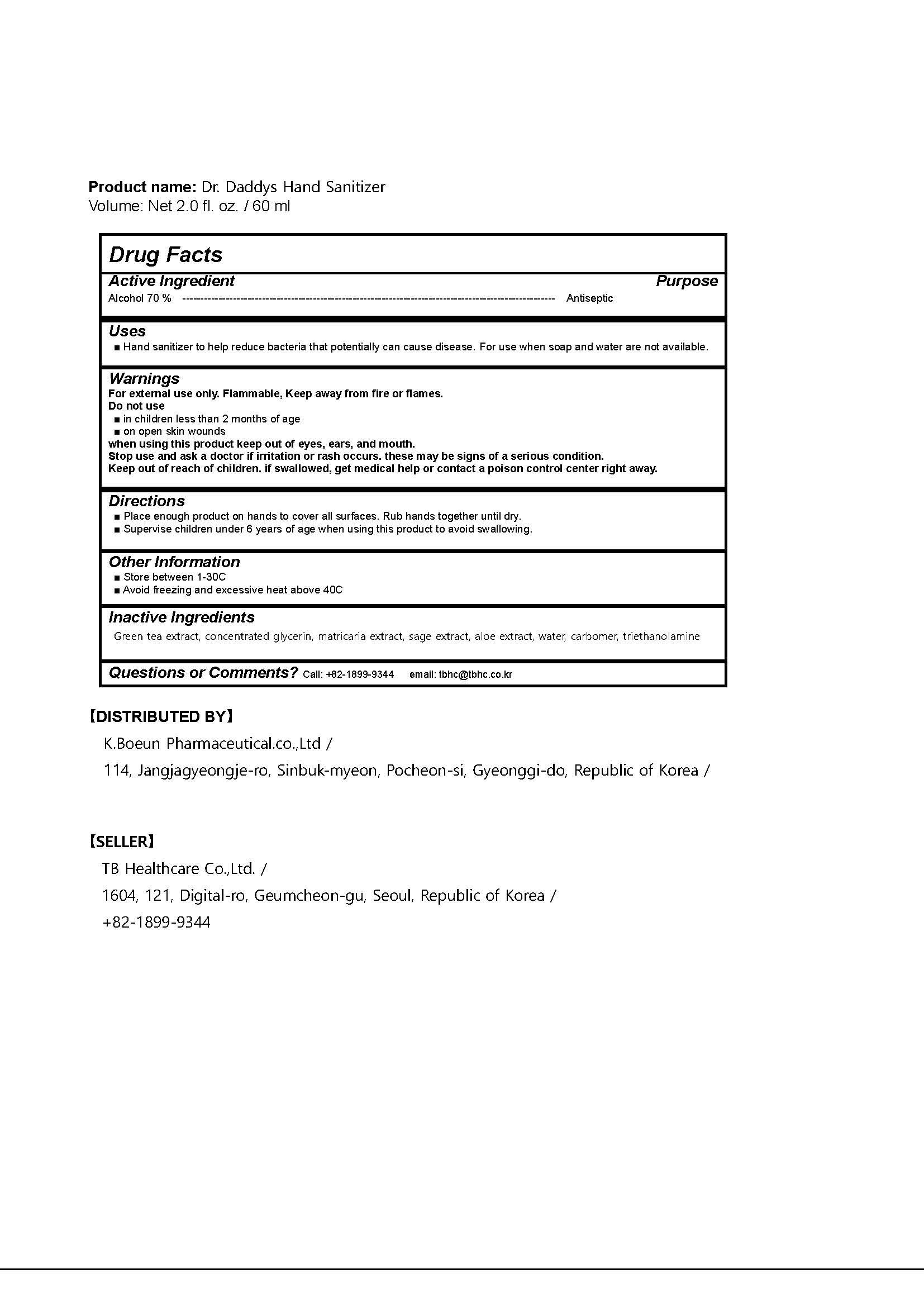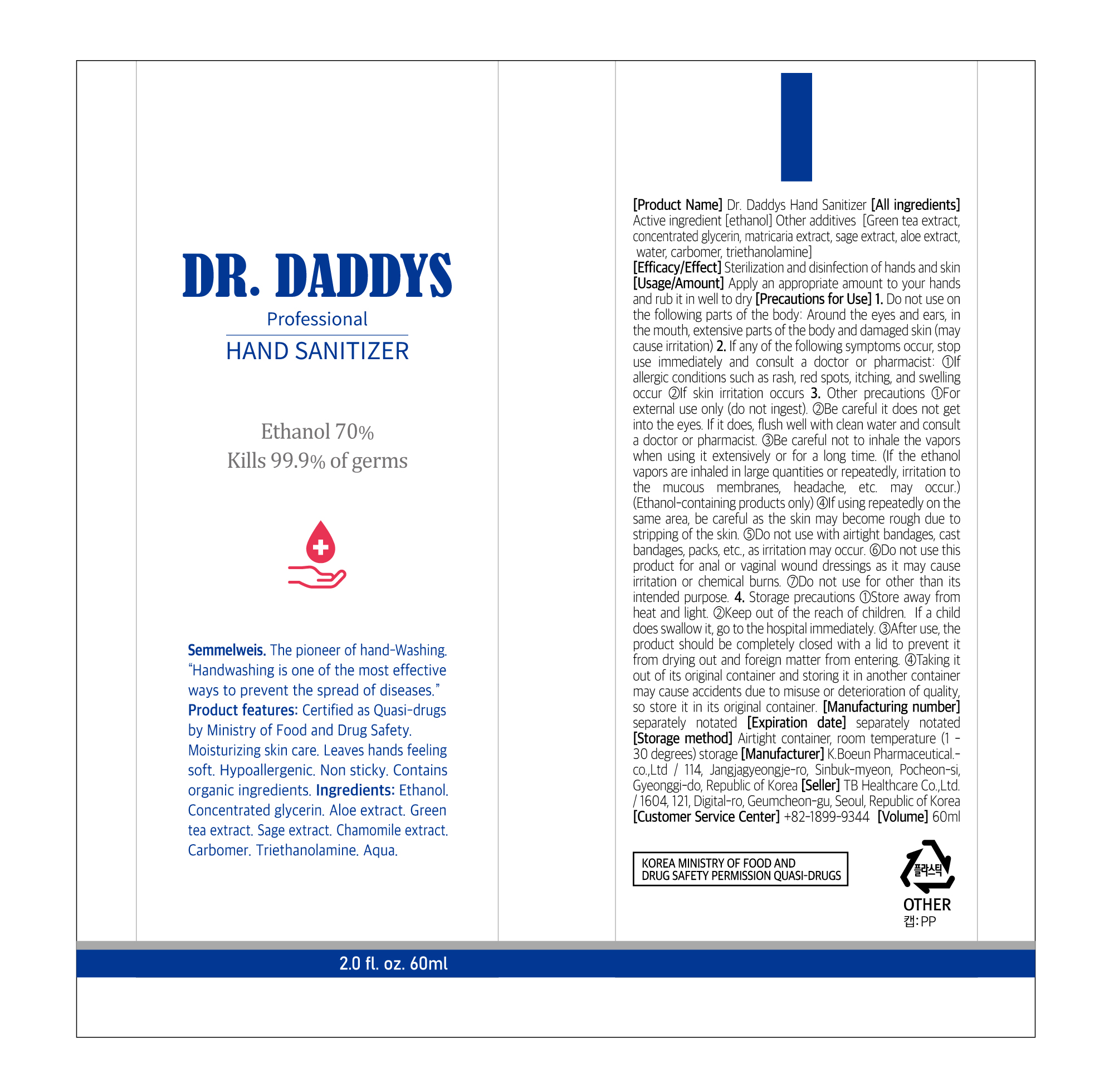 DRUG LABEL: Dr. Daddys Hand Sanitizer
NDC: 76884-0002 | Form: GEL
Manufacturer: TB Healthcare Co., Ltd.
Category: otc | Type: HUMAN OTC DRUG LABEL
Date: 20200512

ACTIVE INGREDIENTS: ALCOHOL 42 mL/60 mL
INACTIVE INGREDIENTS: CARBOMER HOMOPOLYMER, UNSPECIFIED TYPE; GLYCERIN; ALOE; TROLAMINE; WATER; CHAMOMILE; GREEN TEA LEAF

Drug Facts

ACTIVE INGREDIENT

Alcohol

INACTIVE INGREDIENT

Water, Glycerin, Triethanolamine, Carbomer, Green Tea Extract, Aloe Extract, Sage Extract, Matricaria(Chamomilla) Extract

PURPOSE

Antimicrobial

KEEP OUT OF REACH OF THE CHILDREN

INDICATIONS AND USAGE

■ Store between 1-30C

■ Avoid freezing and excessive heat above 40C

WARNINGS

For external use only. Flammable, Keep away from fire or flames.
Do not use

■ in children less than 2 months of age

■ on open skin wounds
when using this product keep out of eyes, ears, and mouth.
Stop use and ask a doctor if irritation or rash occurs. these may be signs of a serious condition.
Keep out of reach of children. if swallowed, get medical help or contact a poison control center right away.

DOSAGE AND ADMINISTRATION

■ Place enough product on hands to cover all surfaces. Rub hands together until dry.

■ Supervise children under 6 years of age when using this product to avoid swallowing.